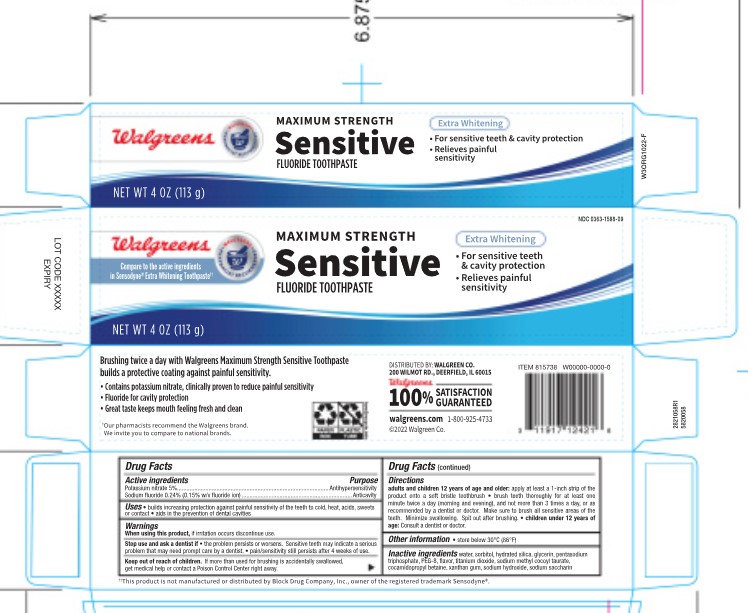 DRUG LABEL: Walgreens Sensitive Extra Whitening
NDC: 0363-1588 | Form: PASTE, DENTIFRICE
Manufacturer: Walgreens
Category: otc | Type: HUMAN OTC DRUG LABEL
Date: 20251121

ACTIVE INGREDIENTS: POTASSIUM NITRATE 5 g/100 g; SODIUM FLUORIDE 0.15 g/100 g
INACTIVE INGREDIENTS: HYDRATED SILICA; TITANIUM DIOXIDE; SODIUM HYDROXIDE; WATER; POLYETHYLENE GLYCOL 400; XANTHAN GUM; COCAMIDOPROPYL BETAINE; SACCHARIN SODIUM; SODIUM TRIPOLYPHOSPHATE ANHYDROUS; SORBITOL; GLYCERIN; SODIUM METHYL COCOYL TAURATE

5820058 Walgreens Sensitive Extra Whitening

ACTIVE INGREDIENT

Potassium Nitrate 5% Antihypersensitivity

Sodium Fluoride 0.24% (0.15% w/v fluoride ion)

INACTIVE INGREDIENT

water, sorbitol, hydrated silica, glycerin, petasodium triphosphate, PEG-8, flavor, titanium dioxide, sodium methyl cocoyl taurate, cocamidopropyl betaine, xanthan gum, sodium hydroxide, sodium saccharin

KEEP OUT OF REACH OF CHILDREN

Kep out of reach of children. If more tahn used for brushing is accidentally swallowed, get medical help or contact a poisoin control center right away.

When using this product, if irritation occurs discontinue use. Stop use and ask a dentist if the problem persists or worsens. Sensitive teeth may indicate a serious problem that may need prompt care by a dentist. Pain/sensitivity still persists after 4 weeks of use.

DOSAGE AND ADMINISTRATION

Builds increasing protection against painful sensitivity of the teeth to cold, heat, acids, sweets or contact. Aids in the prevention of dental cavities.

INDICATIONS AND USAGE

Adults and children 12 years of age and older: apply at least a 1-inch strip of the product onto a soft bristle toothbrush. Brush teeth thoroughly for at least one minute twice a day (morning and evening), and not more than 3 time a day, or as recommended by a dentist or doctor. Make sure to brush all sensitive areas of the teeth. Minimize swallowing. Spit out after brushing. Children under 12 years of age: consult a dentist or doctor.

PURPOSE

Store below 30C (86F).